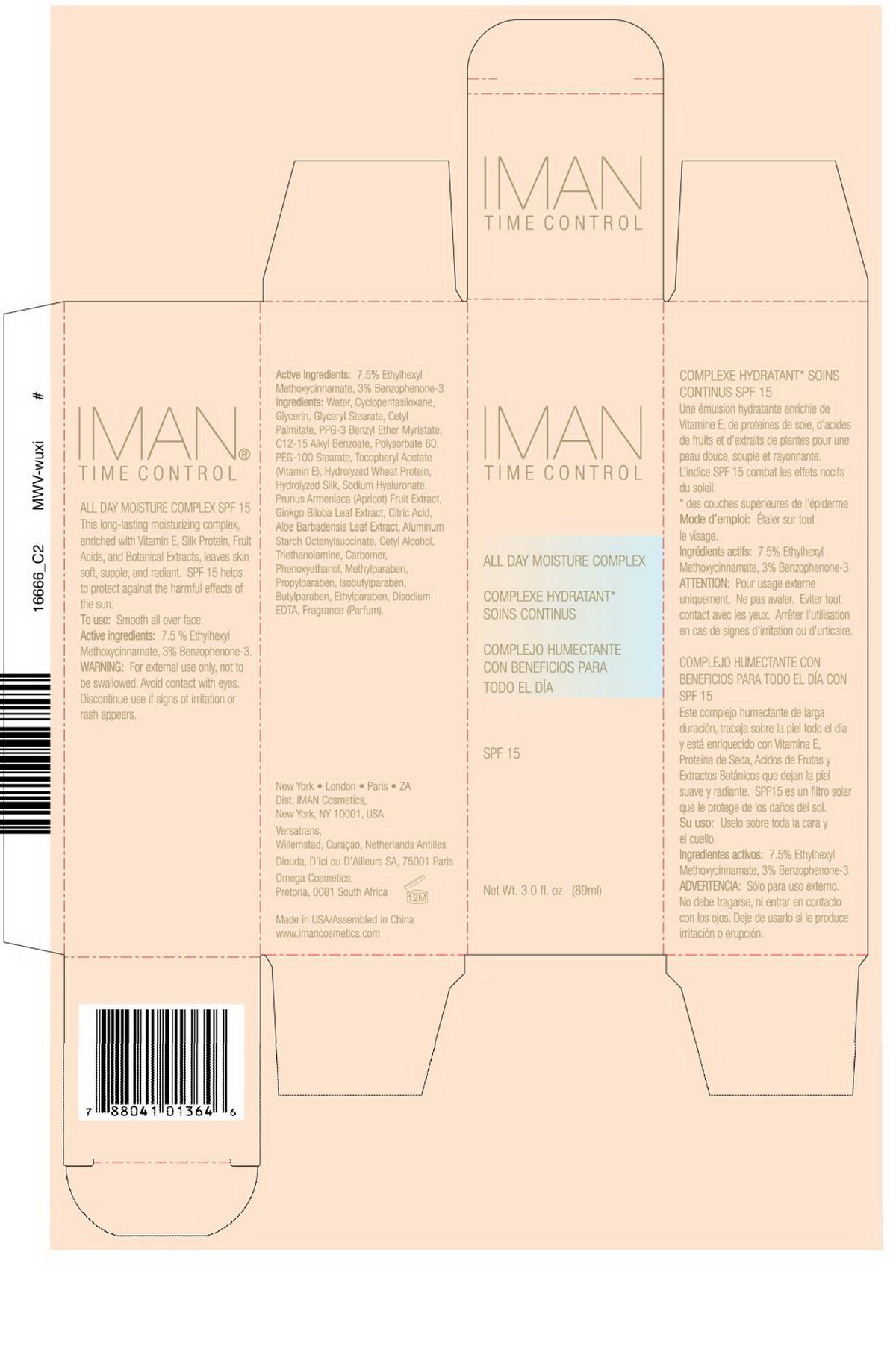 DRUG LABEL: Iman Time Control All Day Moisture Complex SPF 15
NDC: 50950-001 | Form: CREAM
Manufacturer: Sheencolor Biotech Co., Ltd.
Category: otc | Type: HUMAN OTC DRUG LABEL
Date: 20100805

ACTIVE INGREDIENTS: OCTINOXATE 7.5 g/100 g; OXYBENZONE 3 g/100 g
INACTIVE INGREDIENTS: WATER 55.240 g/100 g; CYCLOMETHICONE 5 8 g/100 g; GLYCERIN 5.5 g/100 g; GLYCERYL MONOSTEARATE 5.5 g/100 g; CETYL PALMITATE 3.15 g/100 g; C12-15 ALKYL BENZOATE 1.75 g/100 g; POLYSORBATE 60 1.75 g/100 g; POLYOXYL 100 STEARATE 1.75 g/100 g; ALPHA-TOCOPHEROL ACETATE 0.2 g/100 g; APRICOT SEED OIL 0.05 g/100 g; HYALURONATE SODIUM 0.05 g/100 g; GINKGO 0.05 g/100 g; ANHYDROUS CITRIC ACID 0.01 g/100 g; ALOE VERA LEAF 0.5 g/100 g; ALUMINUM STARCH OCTENYLSUCCINATE 0.8 g/100 g; CETYL ALCOHOL 1 g/100 g; TROLAMINE 0.4 g/100 g; CARBOMER HOMOPOLYMER TYPE A 0.2 g/100 g; PHENOXYETHANOL 0.798 g/100 g; METHYLPARABEN 0.17 g/100 g; PROPYLPARABEN 0.022 g/100 g; ISOBUTYLPARABEN 0.022 g/100 g; BUTYLPARABEN 0.044 g/100 g; ETHYLPARABEN 0.044 g/100 g; EDETATE DISODIUM 0.1 g/100 g; ENGLISH LAVENDER OIL 0.3 g/100 g

Drug Fact

Active Ingredients:

7.5% Ethylhexyl Methoxycinnamate, 3.0% Benzophenone-3

PURPOSE

This long lasting moisturizing complex, enriched with Vitamin E, Silk Protein, Fruit Acids, and Botanic Extracts, leaves skin soft, supple, and radiant.SPF-15 helps to protect against the harmful effect of the sun.

DOSAGE AND ADMINISTRATION

To Use: Smooth all over face

Warnings:

For external use only, not to be swallowed. Avoid contact with eyes. Discontinue use if signs of irritation or rash appear.

Inactive Ingredients

Water, Cyclopentasiloxane, ethyhexyl Methoxycinnamate, Glycerin, Glyceryl Stearate,Cetyl Palmitate,PPG-3 Benyl Ether Myristate, C12-15 Alkyl Benzoate, Polysorbate 60, PEG-100 Stearate, Tocopheryl Acetate (Vitamin E), Hydrolyzed Wheat Protein, Hydrolyzed Silk, Sodium Hyaluronate, Prunus Armeniaca Fruit Extract, Ginkgo Biloba Leaf Extract, Citric Acid, Aloe Barbadensis Leaf Extract, Aluminum Starch, Octenylsuccinate, Cetyl Alcohol, Triethanolamine, Phenoxyethanol, Carbomer, Methylparaben, Propylparaben, Isobutylparaben, Butylparaben, Ethylparaben, Disodium EDTA, Fragrance (Parfum)

label